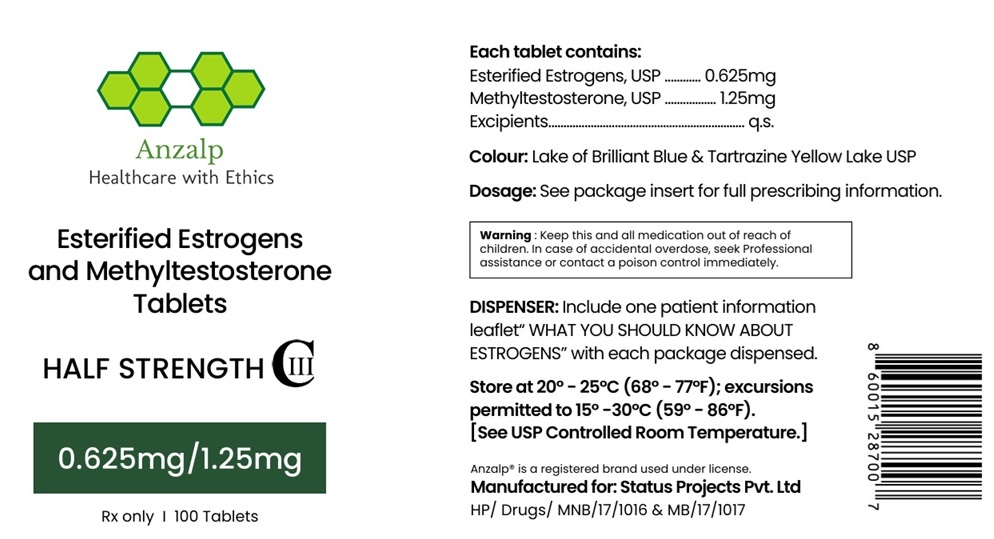 DRUG LABEL: Esterified Estrogens and Methyltestosterone
NDC: 84346-450 | Form: TABLET
Manufacturer: STATUS PROJECTS PRIVATE LIMITED
Category: prescription | Type: HUMAN PRESCRIPTION DRUG LABEL
Date: 20260121
DEA Schedule: CIII

ACTIVE INGREDIENTS: ESTROGENS, ESTERIFIED 0.625 mg/1 1; METHYLTESTOSTERONE 1.25 mg/1 1
INACTIVE INGREDIENTS: ALUMINUM OXIDE; SODIUM CITRATE, UNSPECIFIED FORM; TITANIUM DIOXIDE; TALC; SODIUM BICARBONATE; POLYVINYL ALCOHOL, UNSPECIFIED; FD&C YELLOW NO. 6; FD&C BLUE NO. 1 ALUMINUM LAKE; POLYETHYLENE GLYCOL 400; MAGNESIUM STEARATE; ANHYDROUS LACTOSE; MICROCRYSTALLINE CELLULOSE

Esterified Estrogens and Methyltestosterone Tablets

BOXED WARNING:

1. ESTROGENS HAVE BEEN REPORTED TO INCREASE THE RISK OF ENDOMETRIAL CARCINOMA
Three independent case-control studies have reported an increased risk of endometrial cancer in postmenopausal women exposed to exogenous estrogens for prolonged periods. This risk was independent of the other known risk factors for endometrial cancer. These studies are further supported by the finding that incidence rates of endometrial cancer have increased sharply since 1969 in eight different areas of the United States with population-based cancer reporting systems, an increase which may be related to the rapidly expanding use of estrogens during the last decade.
The three case-control studies reported that the risk of endometrial cancer in estrogen users was about 4.5 to 13.9 times greater than in nonusers. The risk appears to depend on both duration of treatment and estrogen dose. Given these findings, when estrogens are used for the treatment of menopausal symptoms, the lowest dose that will control symptoms should be utilised, and medication should be discontinued as soon as possible. When prolonged treatment is medically indicated, the patient should be reassessed on at least a semiannual basis to determine the need for continued therapy. Although the evidence must be considered preliminary, one study suggests that cyclic administration of low doses of estrogen may carry less risk than continuous administration. It therefore appears prudent to utilise such a regimen.
Close clinical surveillance of all women taking estrogens is important. In all cases of undiagnosed persistent or recurring abnormal vaginal bleeding, adequate diagnostic measures should be undertaken to rule out malignancy.
There is no evidence at present that "natural" estrogens are more or less hazardous than "synthetic" estrogens at equiestrogenic doses.
2. ESTROGENS SHOULD NOT BE USED DURING PREGNANCY
The use of female sex hormones, both estrogens and progestogens, during early pregnancy may seriously damage the offspring. It has been shown that females exposed in utero to diethylstilbestrol, a non-steroidal estrogen, have an increased risk of developing in later life a form of vaginal or cervical cancer that is ordinarily extremely rare. This risk has been estimated as not greater than 4 per 1000 exposures. Furthermore, a high percentage of such exposed women (from 30 to 90 percent) have been found to have vaginal adenosis, epithelial changes of the vagina and cervix. Although these changes are histologically benign, it is not known whether they are precursors of malignancy. Although similar data are not available with the use of other estrogens, it cannot be presumed they would not induce similar changes.
Several reports suggest an association between intrauterine exposure to female sex hormones and congenital anomalies, including congenital heart defects and limb reduction defects. One case control study estimated a 4.7-fold increased risk of limb reduction defects in infants exposed in utero to sex hormones (oral contraceptives, hormone withdrawal tests for pregnancy, or attempted treatment for threatened abortion). Some of these exposures were very short and involved only a few days of treatment. The data suggest that the risk of limb reduction defects in exposed fetuses is somewhat less than 1 per 1000.
In the past, female sex hormones have been used during pregnancy in an attempt to treat threatened or habitual abortion. There is considerable evidence that estrogens are ineffective for these indications, and there is no evidence from well controlled studies that progesterones are effective for these uses.
IF ESTERIFIED ESTROGENS AND METHYLTESTOSTERONE FULL STRENGTH or ESTERIFIED ESTROGENS AND METHYLTESTOSTERONE HALF STRENGTH is used during pregnancy, or if the patient becomes pregnant while taking this drug, she should be apprised of the potential risks to the fetus, and the advisability of pregnancy continuation.

DESCRIPTION

1- Product Name: Esterified Estrogens and Methyltestosterone Tablets

2- Name and Strength of the active Ingredient (s)
Each tablet contains:
Esterified Estrogens, USP......0.625 mg
Methyltestosterone, USP........1.25 mg

3- Product Description
Physical properties
light green, capsule-shaped, oral tablet

4- Pharmacodynamics/ Pharmacokinetics Pharmacotherapeutic group

Estrogens

Estrogens are important in the development and maintenance of the female reproductive system and secondary sex characteristics. They promote growth and development of the vagina, uterus, and fallopian tubes, and enlargement of the breasts. Indirectly, they contribute to the shaping of the skeleton, maintenance of tone and elasticity of urogenital structures, changes in the epiphyses of the long bones that allow for the pubertal growth spurt and its termination, growth of axillary and pubic hair, and pigmentation of the nipples and genitals. Decline of estrogenic activity at the end of the menstrual cycle can bring on menstruation, although the cessation of progesterone secretion is the most important factor in the mature ovulatory cycle. However, in the preovulatory or nonovulatory cycle, estrogen is the primary determinant in the onset of menstruation. Estrogens also affect the release of pituitary gonadotropins. The pharmacologic effects of esterified estrogens are similar to those of endogenous estrogens. They are soluble in water and are well absorbed from the gastrointestinal tract.

In responsive tissues (female genital organs, breasts, hypothalamus, pituitary) estrogens enter the cell and are transported into the nucleus. As a result of estrogen action, specific RNA and protein synthesis occurs.

Estrogen Pharmacokinetics

Metabolism and inactivation occur primarily in the liver. Some estrogens are excreted into the bile; however, they are reabsorbed from the intestine and returned to the liver through the portal venous system. Water soluble esterified estrogens are strongly acidic and are ionized in body fluids, which favor excretion through the kidneys since tubular reabsorption is minimal.

Androgens

Endogenous androgens are responsible for the normal growth and development of the male sex organs and for maintenance of secondary sex characteristics. These effects include the growth and maturation of prostate, seminal vesicles, penis, and scrotum; the development of male hair distribution, such as beard, pubic, chest and axillary hair, laryngeal enlargement, vocal cord thickening, alterations in body musculature, and fat distribution. Drugs in this class also cause retention of nitrogen, sodium, potassium, phosphorus, and decreased urinary excretion of calcium. Androgens have been reported to increase protein anabolism and decrease protein catabolism. Nitrogen balance is improved only when there is sufficient intake of calories and protein. Androgens are responsible for the growth spurt of adolescence and for the eventual termination of linear growth centers. In children, exogenous androgens accelerate linear growth rates, but may cause a disproportionate advancement in bone maturation. Use over long periods may result in fusion of the epiphyseal growth centers and termination of growth process. Androgens have been reported to stimulate the production of red blood cells by enhancing the production of erythropoietic stimulating factor.

Androgen Pharmacokinetics

Testosterone given orally is metabolized by the gut and 44 percent is cleared by the liver in the first pass. Oral doses as high as 400 mg per day are needed to achieve clinically effective blood levels for full replacement therapy. The synthetic androgens (methyltestosterone and fluoxymesterone) are less extensively metabolized by the liver and have longer half-lives. They are more suitable than testosterone for oral administration.

Testosterone in plasma is 98 percent bound to a specific testosterone estradiol binding globulin, and about 2 percent is free. Generally, the amount of this sex-hormone binding globulin in the plasma will determine the distribution of testosterone between free and bound forms, and the free testosterone concentration will determine its half-life.

About 90 percent of a dose of testosterone is excreted in the urine as glucuronic and sulfuric acid conjugates of testosterone and its metabolites; about 6 percent of a dose is excreted in the faeces, mostly in the unconjugated form. Inactivation of testosterone occurs primarily in the liver. Testosterone is metabolized to various 17-keto steroids through two different pathways. There are considerable variations of the half-life of testosterone as reported in the literature, ranging from 10 to 100 minutes.

In many tissues the activity of testosterone appears to depend on reduction to dihydrotestosterone, which binds to cytosol receptor proteins. The steroid-receptor complex is transported to the nucleus where it initiates transcription events and cellular changes related to androgen action.

5- Indication

ESTERIFIED ESTROGENS AND METHYLTESTOSTERONE HALF STRENGTH are indicated in the treatment of: Moderate to severe vasomotor symptoms associated with the menopause in those patients not improved by estrogens alone. (There is no evidence that estrogens are effective for nervous symptoms or depression without associated vasomotor symptoms, and they should not be used to treat such conditions.)

ESTERIFIED ESTROGENS AND METHYLTESTOSTERONE HALF STRENGTH HAVE NOT BEEN SHOWN TO BE EFFECTIVE FOR ANY PURPOSE DURING PREGNANCY AND ITS USE MAY CAUSE SEVERE HARM TO THE FETUS.

6- Recommended Dose

Usual Dosage Range

ESTERIFIED ESTROGENS AND METHYLTESTOSTERONE HALF STRENGTH daily as recommended by the physician.

Treated patients with an intact uterus should be monitored closely for signs of endometrial cancer and appropriate diagnostic measures should be taken to rule out malignancy in the event of persistent or recurring abnormal vaginal bleeding.

7- Recommended route of administration:

Given cyclically for short-term use only:
For treatment of moderate to severe vasomotor symptoms associated with the menopause in patients not improved by estrogen alone.
The lowest dose that will control symptoms should be chosen and medication should be discontinued as promptly as possible. Administration should be cyclic (e.g., three weeks on and one week off). Attempts to discontinue or taper medication should be made at three-to-six-month intervals.

8- Contraindications

Estrogens should not be used in women with any of the following conditions:

1. Known or suspected cancer of the breast except in appropriately selected patients being treated for metastatic disease.

2. Known or suspected estrogen-dependent neoplasia.

3. Known or suspected pregnancy.

4. Undiagnosed abnormal genital bleeding.

5. Active thrombophlebitis or thromboembolic disorders.

6. A past history of thrombophlebitis, thrombosis, or thromboembolic disorders associated with previous estrogen use (except when in treatment of breast malignancy).

Methyltestosterone should not be used in:

1. The presence of severe liver damage.

2. Pregnancy and in breast-feeding mothers because of the possibility of masculinization of the female fetus or breast-fed infant.

9- Warnings and Precautions

Associated with Estrogens

Induction of malignant neoplasms. Long term continuous administration of natural and synthetic estrogens in certain animal species increases this frequency of carcinomas of the breast, cervix, vagina, and liver. There is now evidence that estrogens increase the risk of carcinoma of the endometrium in humans.

At the present time there is no satisfactory evidence that estrogens given to postmenopausal women increase the risk of cancer of the breast,18 although a recent long-term follow-up of a single physician's practice has raised this possibility.18a Because of the animal data, there is a need for caution in prescribing estrogens for women with a strong family history of breast cancer or who have breast nodules, fibrocystic disease, or abnormal mammograms.

Gallbladder disease. A recent study has reported a 2 to 3-fold increase in the risk of surgically confirmed gallbladder disease in women receiving postmenopausal estrogens,18 similar to the 2-fold increase previously noted in users of oral contraceptives as in the case of oral contraceptives the increased risk appeared after two years of use.
Effects similar to those caused by estrogen-progesterone oral contraceptives. There are several serious adverse effects of oral contraceptives, most of which have not, up to now, been documented as consequences of postmenopausal estrogen therapy. This may reflect the comparatively low doses of estrogen used in postmenopausal women. It would be expected that the larger doses of estrogen used to treat prostatic or breast cancer or postpartum breast engorgement are more likely to result in these adverse effects, and, in fact, it has been shown that there is an increased risk of thrombosis in men receiving estrogens for prostatic cancer and women for postpartum breast engorgement.

a. Thromboembolic disease. It is now well established that users of oral contraceptives have an increased risk of various thromboembolic and thrombotic vascular diseases, such as thrombophlebitis, pulmonary embolism, stroke, and myocardial infarction. Cases of retinal thrombosis, mesenteric thrombosis, and optic neuritis have been reported in oral contraceptive users. There is evidence that the risk of several of these adverse reactions is related to the dose of the drug. An increased risk of post- surgery thromboembolic complications has also been reported in users of oral contraceptives. If feasible, estrogen should be discontinued at least 4 weeks before surgery of the type associated with an increased risk of thromboembolism, or during periods of prolonged immobilization.

While an increased rate of thromboembolic and thrombotic disease in postmenopausal users of estrogens has not been found, this does not rule out the possibility that such an increase may be present or that subgroups of women who have underlying risk factors or who are receiving relatively large doses of estrogens may have increased risk. Therefore, estrogens should not be used in persons with active thrombophlebitis or thromboembolic disorders, and they should not be used (except in treatment of malignancy) in persons with a history of such disorders in association with estrogen use. They should be used with caution in patients with cerebral vascular or coronary artery disease and only for those in whom estrogens are clearly needed.

Large doses of estrogen (5 mg esterified estrogens per day), comparable to those used to treat cancer of the prostate and breast, have been shown in a large prospective clinical trial in men to increase the risk of nonfatal myocardial infarction, pulmonary embolism and thrombophlebitis. When estrogen doses of this size are used, any of the thromboembolic and thrombotic adverse effects associated with oral contraceptive use should be considered a clear risk.

b. Hepatic adenoma. Benign hepatic adenomas appear to be associated with the use of oral contraceptives. Although benign and rare, these may rupture and may cause death through intra-abdominal hemorrhage. Such lesions have not yet been reported in association with other estrogen or progestogen preparations but should be considered in estrogen users having abdominal pain and tenderness, abdominal mass, or hypovolemic shock. Hepatocellular carcinoma has also been reported in women taking estrogen- containing oral contraceptives. The relationship of this malignancy to these drugs is not known at this time.

c. Elevated blood pressure. Increased blood pressure is not uncommon in women using oral contraceptives. There is now a report that this may occur with use of estrogens in the menopause and blood pressure should be monitored with estrogen use, especially if high doses are used.

d. Glucose tolerance. A worsening of glucose tolerance has been observed in a significant percentage of patients of estrogen- containing oral contraceptives. For this reason, diabetic patients should be carefully observed while receiving estrogens.

Hypercalcemia. Administration of estrogens may lead to severe hypercalcemia in patients with breast cancer and bone metastases. If this occurs, the drug should be stopped and appropriate measures taken to reduce the serum calcium level.

Associated with Methyltestosterone

In patients with breast cancer, androgen therapy may cause hypercalcemia by stimulating osteolysis. In this case the drug should be discontinued.

Prolonged use of high doses of androgens has been associated with the development of peliosis hepatis and hepatic neoplasms including hepatocellular carcinoma. (See PRECAUTIONS – Carcinogenesis).

Peliosis hepatis can be a life-threatening or fatal complication.

Cholestatic hepatitis and jaundice occur with 17-alpha-alkylandrogens at a relatively low dose. If cholestatic hepatitis with jaundice appears or if liver function tests become abnormal, the androgen should be discontinued and the etiology should be determined.
Drug-induced jaundice is reversible when the medication is discontinued.

Edema with or without heart failure may be a serious complication in patients with preexisting cardiac, renal, or hepatic disease. In addition to discontinuation of the drug, diuretic therapy may be required.

Precautions

Associated with Estrogens

A. General Precautions

A complete medical and family history should be taken prior to the initiation of any estrogen therapy. The pretreatment and periodic physical examinations should include special reference to blood pressure, breasts, abdomen, and pelvic organs, and should include a Papanicolaou smear. As a general rule, estrogen should not be prescribed for longer than one year without another physical examination being performed.
Fluid retention– Because estrogens may cause some degree of fluid retention, conditions which might be influenced by this factor such as asthma, epilepsy, migraine, and cardiac or renal dysfunction, require careful observation.
Certain patients may develop undesirable manifestations of excessive estrogenic stimulation, such as abnormal or excessive uterine bleeding, mastodynia, etc.
Oral contraceptives appear to be associated with an increased incidence of mental depression. Although it is not clear whether this is due to the estrogenic or progestogenic component of the contraceptive, patients with a history of depression should be carefully observed.
Preexisting uterine leiomyomata may increase in size during estrogen use.
The pathologist should be advised of estrogen therapy when relevant specimens are submitted.
Patients with a past history of jaundice during pregnancy have an increased risk of recurrence of jaundice while receiving estrogen- containing oral contraceptive therapy. If jaundice develops in any patient receiving estrogen, the medication should be discontinued while the cause is investigated.
Estrogens may be poorly metabolized in patients with impaired liver function and they should be administered with caution in such patients.
Because estrogens influence the metabolism of calcium and phosphorus, they should be used with caution in patients with metabolic bone diseases that are associated with hypercalcemia or in patients with renal insufficiency.
Because of the effects of estrogens on epiphyseal closure, they should be used judiciously in young patients in whom bone growth is not complete.
Certain endocrine and liver function tests may be affected by estrogen-containing oral contraceptives. The following similar changes may be expected with larger doses of estrogen:

a. Increased sulfobromophthalein retention.
b. Increased prothrombin and factors VII, VIII, IX and X; decreased antithrombin 3: increased norepinephrine induced platelet aggregability.
c. Increased thyroid binding globulin (TBG) leading to increased circulating total thyroid hormone, as measured by PBI, T4 by column, or T4 by radioimmunoassay. Free T3 resin uptakes is decreased, reflecting the elevated TBG; free T4 concentration is unaltered.
d. Impaired glucose tolerance.
e. Decreased pregnanediol excretion.
f. Reduced response to metyrapone test.
g. Reduced serum folate concentration.
h. Increased serum triglyceride and phospholipid concentration.

B. Pregnancy Category X

See CONTRAINDICATIONS.

C. Nursing Mothers

As a general principle, the administration of any drug to nursing mothers should be done only when clearly necessary since many drugs are excreted in human milk.

GENERAL PRECAUTIONS

Associated with Methyltestosterone

A. General Precautions

Women should be observed for signs of virilization (deepening of the voice, hirsutism, acne, clitoromegaly, and menstrual irregularities). Discontinuation of drug therapy at the time of evidence of mild virilism is necessary to prevent irreversible virilization. Such virilization is usual following androgen use at high doses.
Prolonged dosage of androgen may result in sodium and fluid retention. This may present a problem, especially in patients with compromised cardiac reserve or renal disease.
Hypersensitivity may occur rarely.
PBI may be decreased in patients taking androgens.
Hypercalcemia may occur. If this does occur, the drug should be discontinued.

B. Information for the Patient

The physician should instruct patients to report any of the following side effects of androgens:
Women: Hoarseness, acne, changes in menstrual periods, or more hair on the face.
All Patients: Any nausea, vomiting, changes in skin color of ankle swelling.

C. Laboratory Tests

Women with disseminated breast carcinoma should have frequent determination of urine and serum calcium levels during the course of androgen therapy.
Because of the hepatotoxicity associated with the use of 17-alpha-alkylated androgens, liver function tests should be obtained periodically.
Hemoglobin and hematocrit should be checked periodically for polycythemia in patients who are receiving high doses of androgens.

D. Drug Interactions

Anticoagulants C-17 substituted derivatives of testosterone, such as methandrostenolone, have been reported to decrease the anticoagulant requirements of patients receiving oral anticoagulants. Patients receiving oral anticoagulant therapy require close monitoring, especially when androgens are started or stopped.
Oxyphenbutazone. Concurrent administration of oxyphenbutazone and androgens may result in elevated serum levels of oxyphenbutazone.
Insulin. In diabetic patients the metabolic effects of androgens may decrease blood glucose and insulin requirements.

E. Drug/Laboratory Test Interferences

Androgens may decrease levels of thyroxine-binding globulin, resulting in decreased T4 serum levels and increased resin uptake of T3 and T4. Free thyroid hormone levels remain unchanged, however, and there is no clinical evidence of thyroid dysfunction.

F. Carcinogenesis

Animal Data. Testosterone has been tested by subcutaneous injection and implantation in mice and rats. The implant induced cervical-uterine tumours in mice, which metastasized in some cases. There is suggestive evidence that injection of testosterone into some strains of female mice increases their susceptibility to hepatoma. Testosterone is also known to increase the number of tumours and decrease the degree of differentiation of chemically induced carcinomas of the liver in rats.

Human Data. There are rare reports of hepatocellular carcinoma in patients receiving long-term therapy with androgens in high doses. Withdrawal of the drugs did not lead to regression of the tumours in all cases.

Geriatric Patients treated with androgens may be at an increased risk for the development of prostatic hypertrophy and prostatic carcinoma.

G. Pregnancy

Teratogenic Effects. Pregnancy Category X (see CONTRAINDICATIONS).

H. Nursing Mothers

It is not known whether androgens are excreted in human milk. Because many drugs are excreted in human milk and because of the potential for serious adverse reactions in nursing infants from androgens, a decision should be made whether to discontinue nursing or to discontinue the drug, taking into account the importance of the drug to the mother.

10- Undesirable Effects

Associated with Estrogens

(See Warnings regarding induction of neoplasia, adverse effects on the fetus, increased incidence of gallbladder disease, and adverse effects similar to those of oral contraceptives, including thromboembolism). The following additional adverse reactions have been reported with estrogenic therapy, including oral contraceptives:

Genitourinary system.

Breakthrough bleeding, spotting, change in menstrual flow.
Dysmenorrhea.
Premenstrual-like syndrome.
Amenorrhea during and after treatment.
Increase in size of uterine fibromyomata.
Vaginal candidiasis.
Change in cervical erosion and in degree of cervical secretion.
Cystitis-like syndrome.

Breasts.

Tenderness, enlargement, secretion.

Gastrointestinal.

Nausea, vomiting.
Abdominal cramps, bloating.
Cholestatic jaundice

Skin.

Chloasma or melasma which may persist when drug is discontinued.
Erythema multiforme.
Erythema nodosum.
Hemorrhagic eruption.
Loss of scalp hair.
Hirsutism.

Eyes.

Steepening of corneal curvature.
Intolerance to contact lenses.

CNS.

Headache, migraine, dizziness.
Mental depression.
Chorea.

Miscellaneous.

Increase or decrease in weight.
Reduced carbohydrate tolerance.
Aggravation of porphyria.
Edema.

Changes in libido.

Associated with Methyltestosterone

A. Endocrine and Urogenital.

Female: The most common side effects of androgen therapy are amenorrhea and other menstrual irregularities, inhibition of gonadotropin secretion, and virilization, including deepening of the voice and clitoral enlargement. The latter usually is not reversible after androgens are discontinued. When administered to a pregnant woman androgens cause virilization of external genitalia of the female fetus.
Skin and Appendages: Hirsutism, male pattern of baldness, and acne.
Fluid and Electrolyte Disturbances: Retention of sodium, chloride, water, potassium, calcium, and inorganic phosphates.
Gastrointestinal: Nausea, cholestatic jaundice, alterations in liver function test, rarely hepatocellular neoplasms, and peliosis hepatis.
Hematologic: Suppression of clotting factors, II, V, VII, and X, bleeding in patients on concomitant anticoagulant therapy, and polycythemia.
Nervous System: Increased or decreased libido, headache, anxiety, depression, and generalized paresthesia.
Metabolic: Increased serum cholesterol.
Miscellaneous: Inflammation and pain at site of intramuscular injection or subcutaneous implantation of testosterone containing pellets, stomatitis with buccal preparations, and rarely anaphylactoid reactions.

11- Overdose and Treatment

Numerous reports of ingestion of large doses of estrogen-containing oral contraceptives by young children indicate that serious ill effects do not occur. Overdosage of estrogen may cause nausea, and withdrawal bleeding may occur in females.

There have been no reports of acute overdosage with the androgens.

12- Packaging and storage condition

ESTERIFIED ESTROGENS AND METHYLTESTOSTERONE TABLETS Half Strength in bottles of 100.

ESTERIFIED ESTROGENS AND METHYLTESTOSTERONE TABLETS Half Strength Green, capsule-shaped, oral tablet.
Contains: 0.625 mg of Esterified Estrogens, USP and 1.25 mg of Methyltestosterone, USP.

Store at 20°-25°C (68°-77°F); excursions permitted to 15°-30°C (59°-86°F). [See USP Controlled Room Temperature.]
Rx only

Anzalp
Healthcare with Ethics

CIII
Colour: Lake of Brilliant Blue & Tartrazine Yellow Lake USP

Dosage: See package insert for full prescribing information.

Warning : Keep this and all medication out of reach of children. In case of accidental overdose, seek Professional assistance or contact a poison control immediately.

DISPENSER: Include one patient information leaflet "WHAT YOU SHOULD KNOW ABOUT ESTROGENS" with each package dispensed.

Anzalp® is a registered brand used under license.

Manufactured for: Status Projects Pvt. Ltd